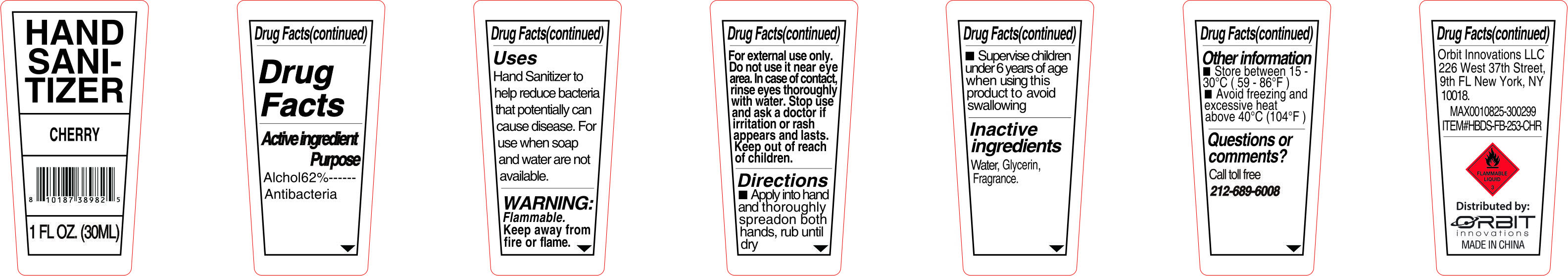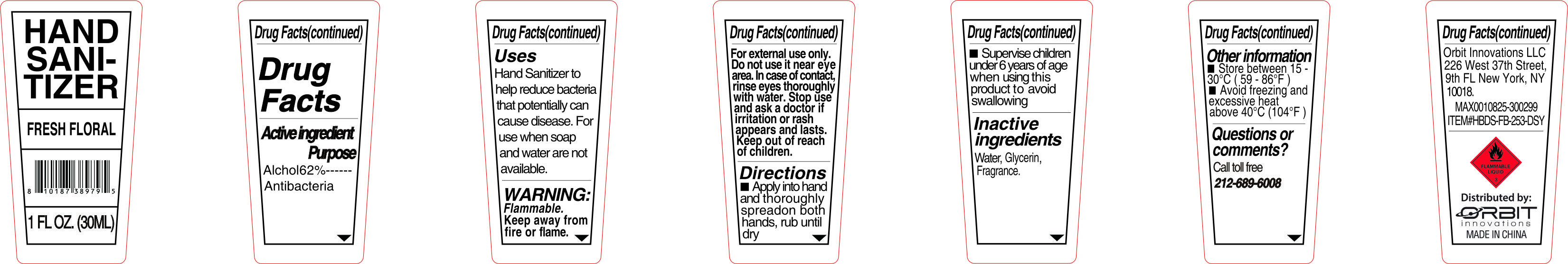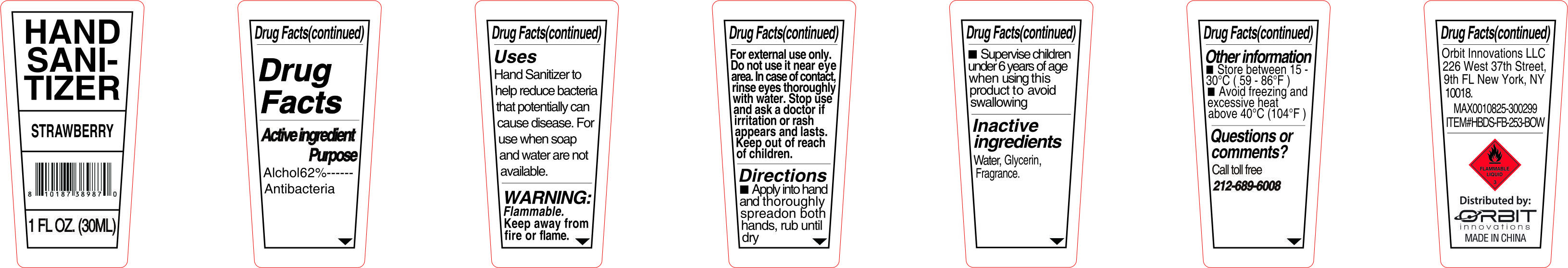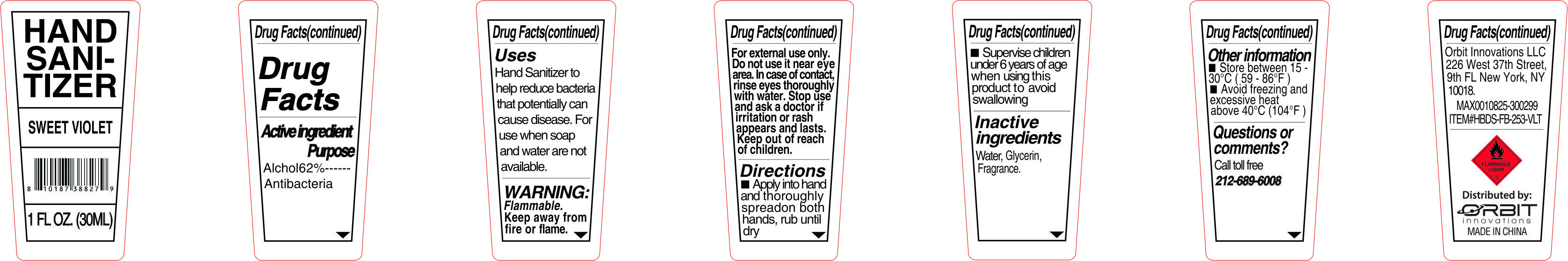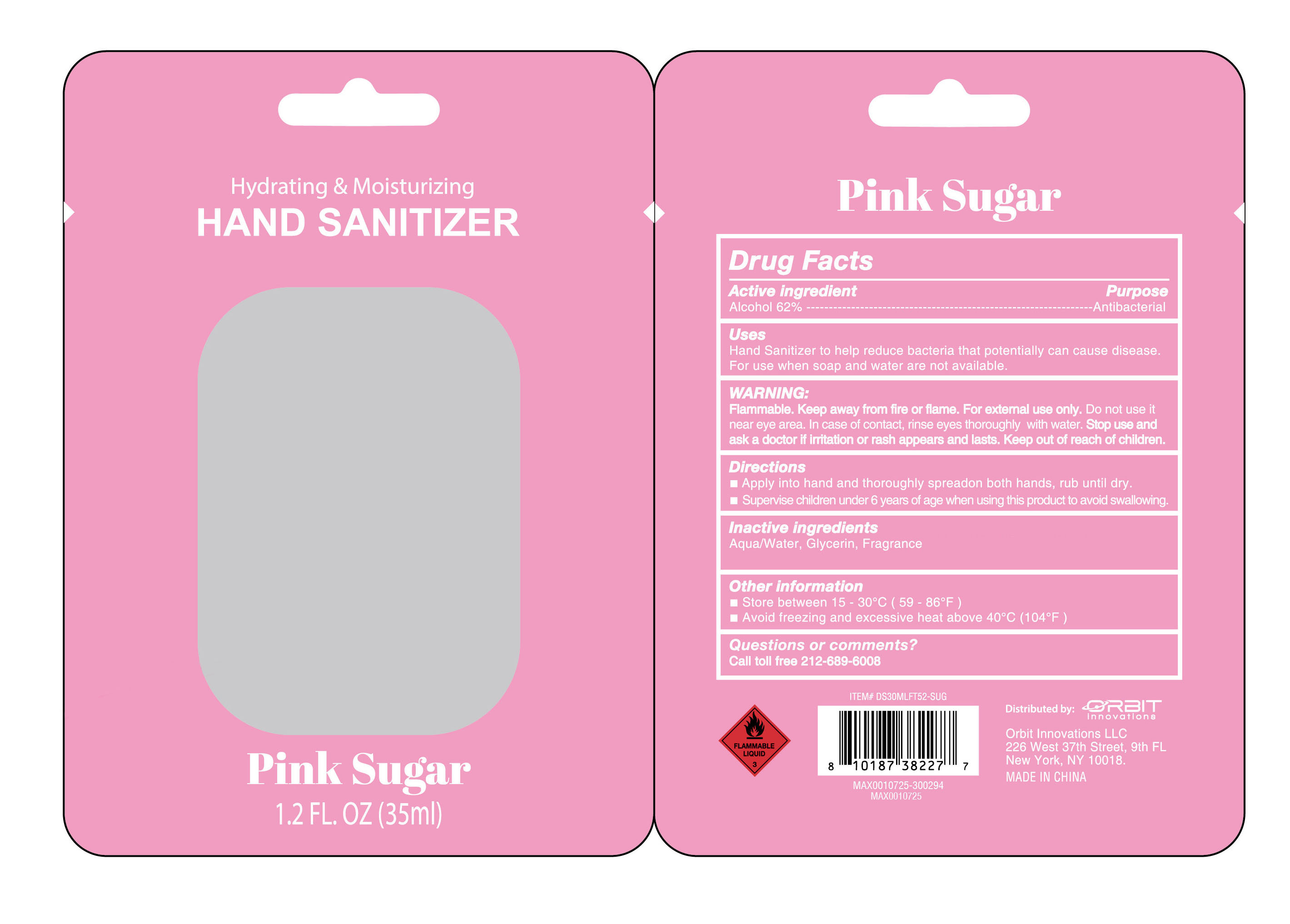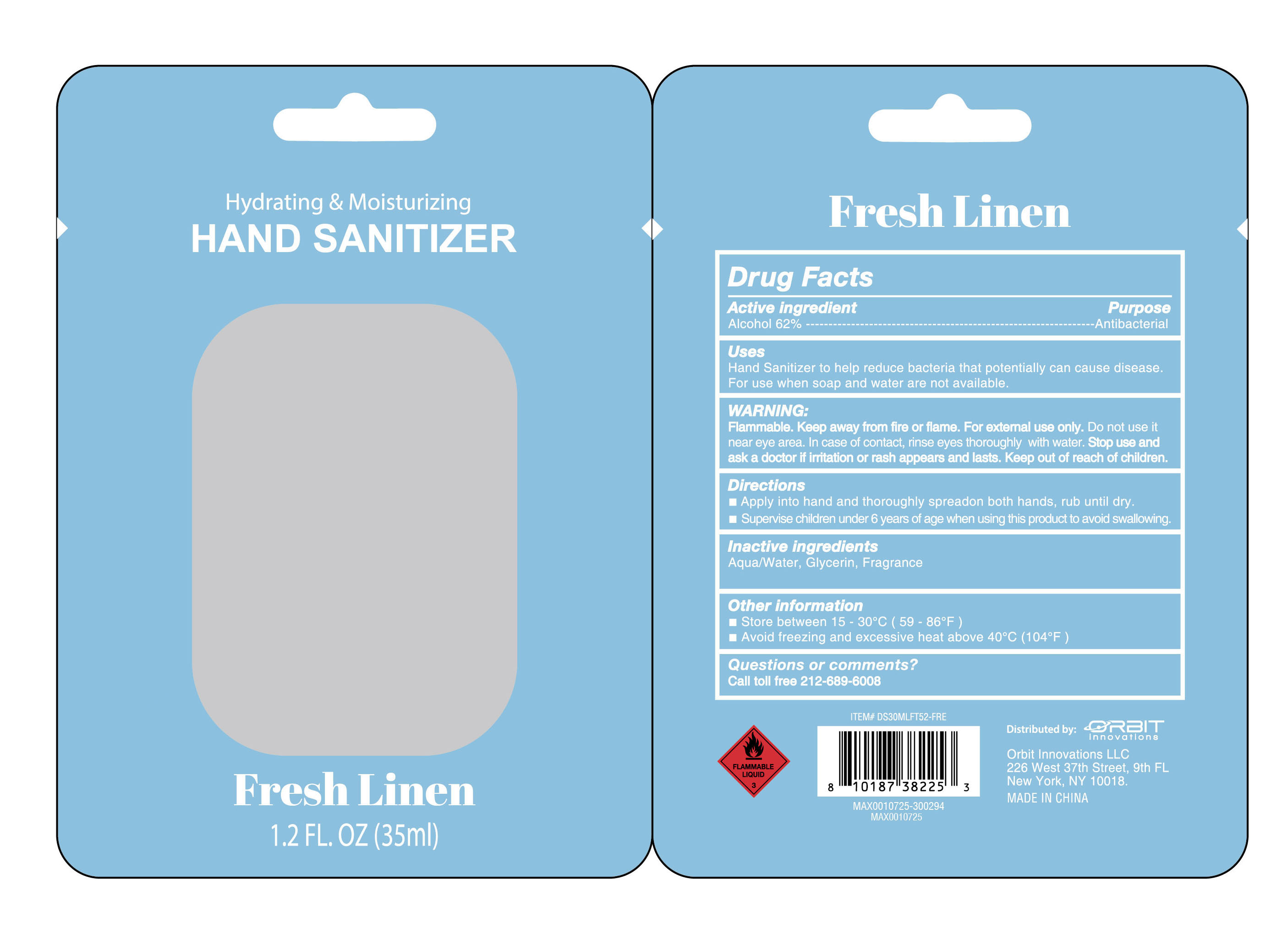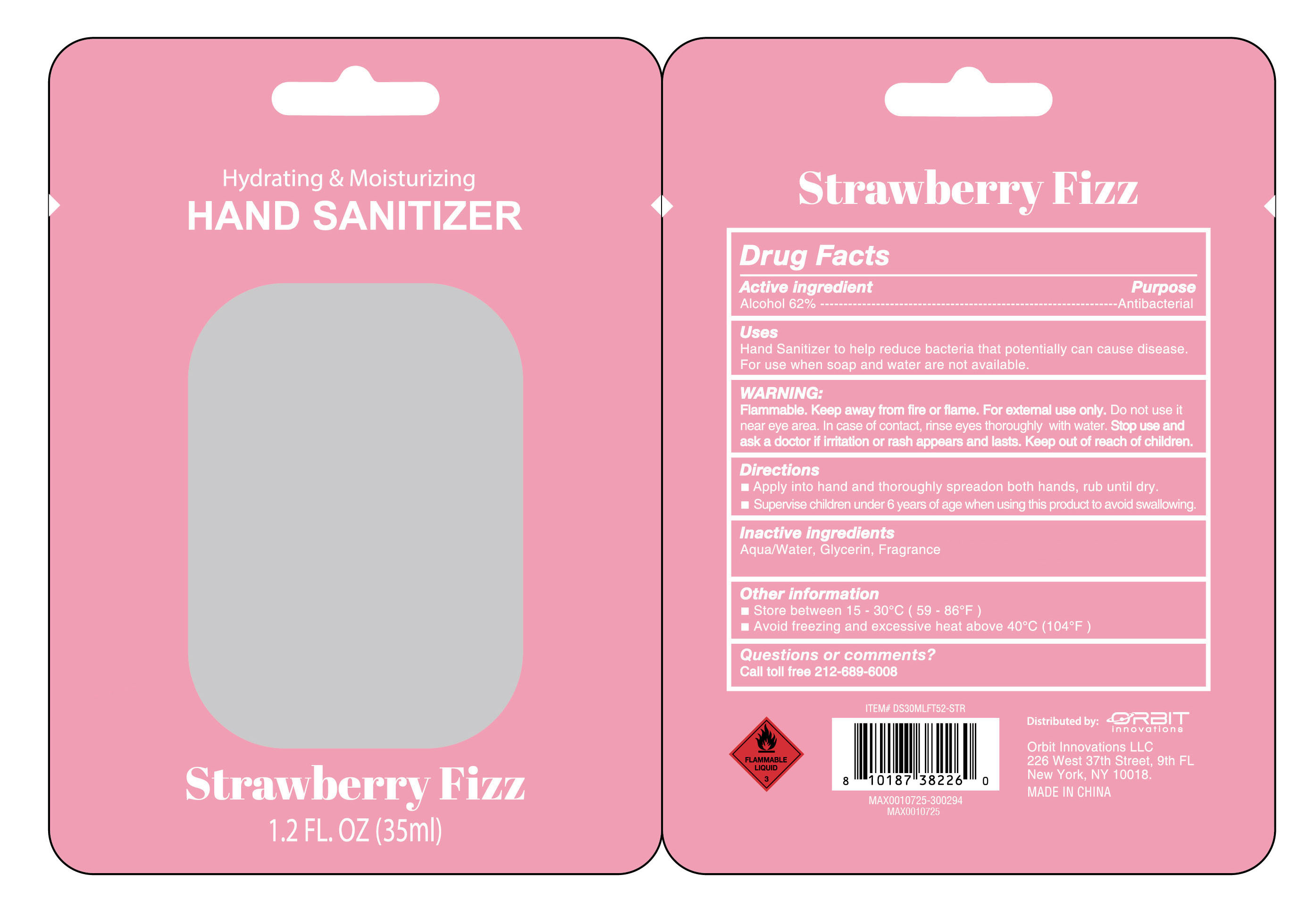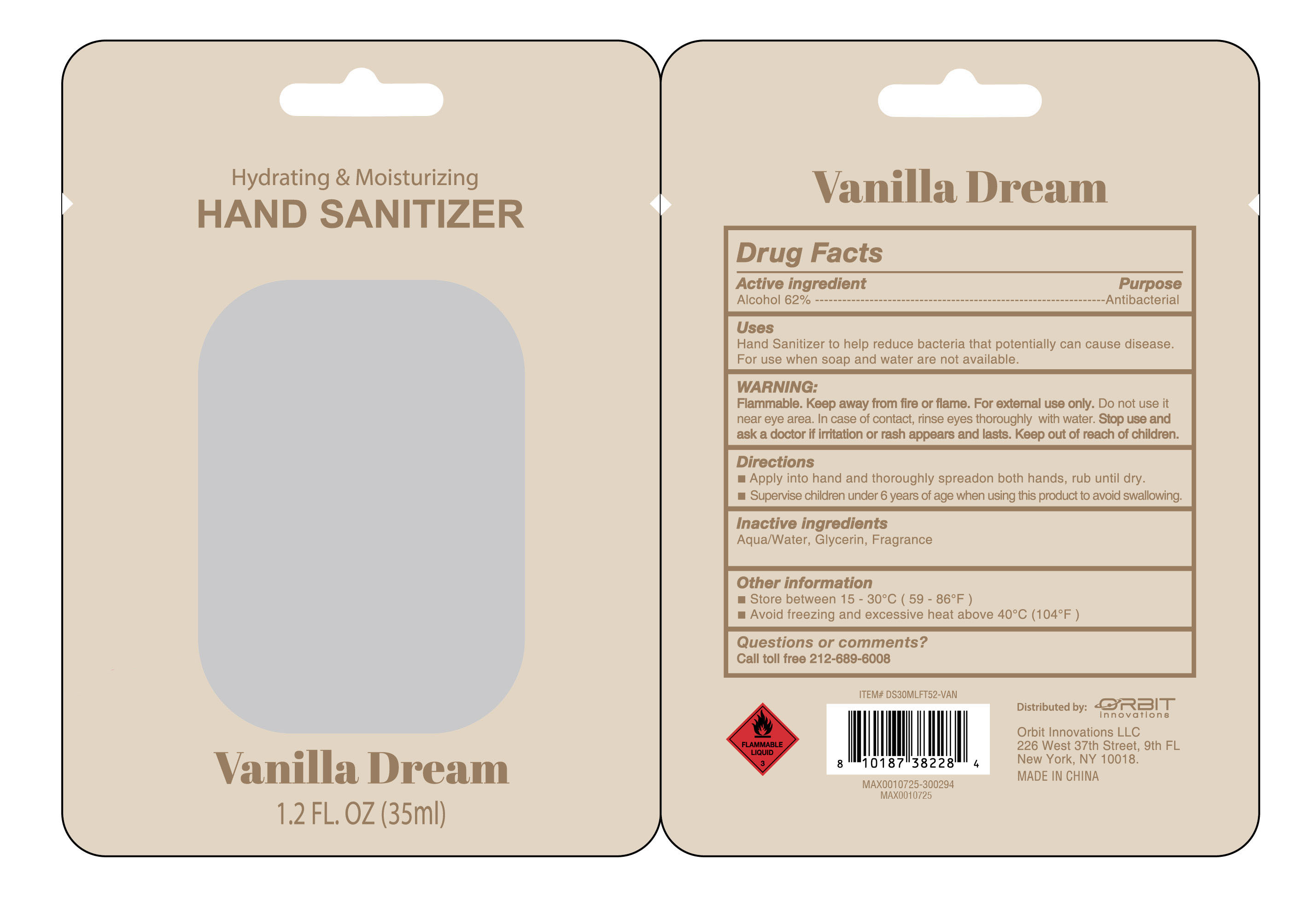 DRUG LABEL: HAND SANITIZER
NDC: 85279-005 | Form: GEL
Manufacturer: Guangdong bangze medicine co., ltd
Category: otc | Type: HUMAN OTC DRUG LABEL
Date: 20260116

ACTIVE INGREDIENTS: ALCOHOL 62 g/100 mL
INACTIVE INGREDIENTS: FRAGRANCE 13576; AQUA; GLYCERIN

85279-005

Active Ingredient(s)

Alcohol 62%

Purpose

Antibacterial

Use

Hand Sanitizer to help reduce bacteria that potentially can cause disease. For use when soap and water are not available.

Warnings

Flammable. Keep away from fire or flame. For extermnal use only.

Do not use it near eye area. In case of contact, rinse eyes thoroughly with water.

When using this product keep out of eyes, In case of contact with eyes, rinse eyes thoroughly with water.

Stop use and ask a doctor if initation or rash appears and lasts

Keep out of reach of children.

Directions

■Apply into hand and thoroughly spreadon both hands, rub until dry.
■Supervise children under 6 years of age when using this product to avoid swallowing.

Other information

■Store between 15- 30°C (59 - 86°F)
■Avoid freezing and excessive heat above 40°C (104°F)

Inactive ingredients

Aqua/Water, Glycerin, Fragrance